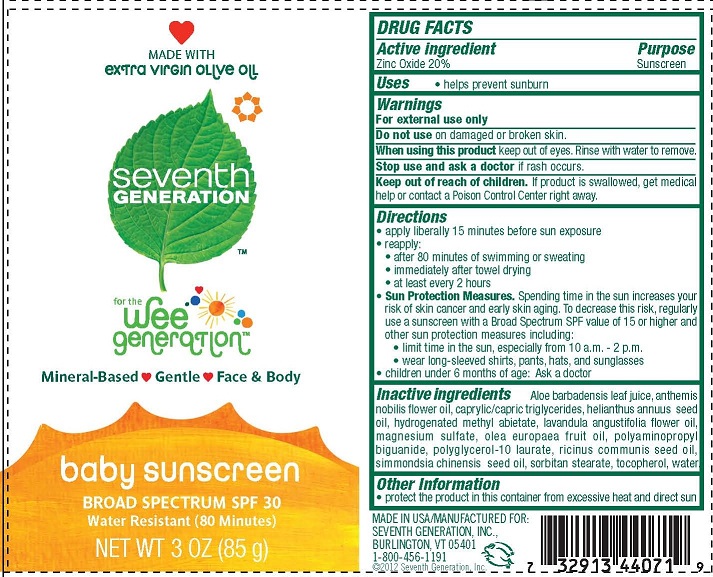 DRUG LABEL: BABY SUNSCREEN
NDC: 42263-101 | Form: LOTION
Manufacturer: SEVENTH GENERATION INC
Category: otc | Type: HUMAN OTC DRUG LABEL
Date: 20120326

ACTIVE INGREDIENTS: ZINC OXIDE 20 g/100 g
INACTIVE INGREDIENTS: ALOE; CHAMAEMELUM NOBILE FLOWER OIL; MEDIUM-CHAIN TRIGLYCERIDES; SUNFLOWER OIL; LAVENDER OIL; MAGNESIUM SULFATE; OLIVE OIL; POLYAMINOPROPYL BIGUANIDE; POLYGLYCERYL-10 OLEATE; CASTOR OIL; JOJOBA OIL; SORBITAN MONOSTEARATE; TOCOPHEROL; WATER

BABY SUNSCREEN

ACTIVE INGREDIENT

ZINC OXIDE 20%

PURPOSE

SUNSCREEN

Other Information
• protect the product in this container from excessive heat and direct sun

Warnings
For external use only

Do not use on damaged or broken skin.

When using this product keep out of eyes. Rinse with water to remove.

Stop use and ask a doctor if rash occurs.

Keep out of reach of children. If product is swallowed, get medical
help or contact a Poison Control Center right away.

Directions
• apply liberally 15 minutes before sun exposure
• reapply:
• after 80 minutes of swimming or sweating
• immediately after towel drying
• at least every 2 hours

OTHER SAFETY INFORMATION

Sun Protection Measures. Spending time in the sun increases your
risk of skin cancer and early skin aging. To decrease this risk, regularly
use a sunscreen with a Broad Spectrum SPF value of 15 or higher and
other sun protection measures including:
• limit time in the sun, especially from 10 a.m. - 2 p.m.
• wear long-sleeved shirts, pants, hats, and sunglasses

PEDIATRIC USE

- CHILDREN UNDER 6 MONTHS OF AGE: ASK A DOCTOR

Inactive ingredients Aloe barbadensis leaf juice, anthemis
nobilis flower oil, caprylic/capric triglycerides, helianthus annuus seed
oil, hydrogenated methyl abietate, lavandula angustifolia flower oil,
magnesium sulfate, olea europaea fruit oil, polyaminopropyl
biguanide, polyglycerol-10 laurate, ricinus communis seed oil,
simmondsia chinensis seed oil, sorbitan stearate, tocopherol, water.

Other Information
• protect the product in this container from excessive heat and direct sun

PACKAGE LABEL

SEVENTH GENERATION
FOR THE WEE GENERATION
BABY SUNSCREEN
BROAD SPECTRUM SPF 30